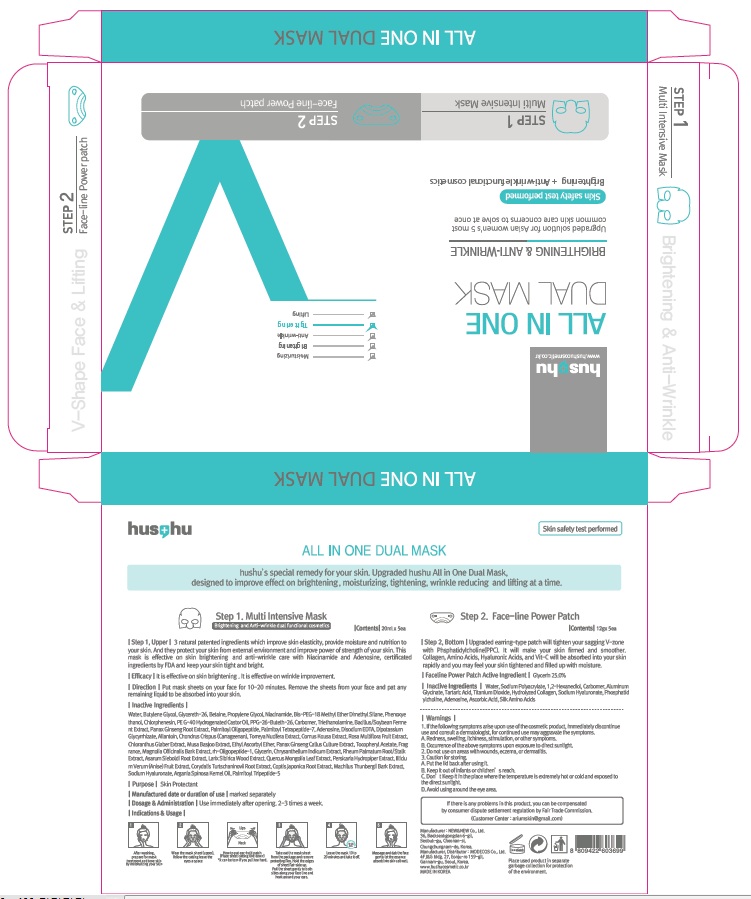 DRUG LABEL: ALL IN ONE DUAL MASK
NDC: 70566-040 | Form: PATCH
Manufacturer: MODECOS CO., LTD.
Category: otc | Type: HUMAN OTC DRUG LABEL
Date: 20160329

ACTIVE INGREDIENTS: Glycerin 3 g/10 1
INACTIVE INGREDIENTS: Water

ACTIVE INGREDIENT

Faceline Power Patch Active Ingredient: Glycerin 25.0%

INACTIVE INGREDIENT

Multi Intensive Mask Inactive Ingredients: Water, Butylene Glycol, Glycereth-26, Betaine, Propylene Glycol, Niacinamide, Bis-PEG-18 Methyl Ether Dimethyl Silane, Phenoxyethanol, Chlorphenesin, PEG-40 Hydrogenated Castor Oil, PPG-26-Buteth-26, Carbomer, Triethanolamine, Bacillus/Soybean Ferment Extract, Panax Ginseng Root Extract, Palmitoyl Oligopeptide, Palmitoyl Tetrapeptide-7, Adenosine, Disodium EDTA, Dipotassium Glycyrrhizate, Allantoin, Chondrus Crispus (Carrageenan), Torreya Nucifera Extract, Cornus Kousa Extract, Rosa Multiflora Fruit Extract, Chloranthus Glaber Extract, Musa Basjoo Extract, Ethyl Ascorbyl Ether, Panax Ginseng Callus Culture Extract, Tocopheryl Acetate, Fragrance, Magnolia Officinalis Bark Extract, rh-Oligopeptide-1, Glycerin, Chrysanthellum Indicum Extract, Rheum Palmatum Root/Stalk Extract, Asarum Sieboldi Root Extract, Larix Sibirica Wood Extract, Quercus Mongolia Leaf Extract, Persicaria Hydropiper Extract, Illicium Verum (Anise) Fruit Extract, Corydalis Turtschaninovii Root Extract, Coptis Japonica Root Extract, Machilus Thunbergii Bark Extract, Sodium Hyaluronate, Argania Spinosa Kernel Oil, Palmitoyl Tripeptide-5

Faceline Power Patch Inactive Ingredients: Water, Sodium Polyacrylate, 1,2-Hexanediol, Carbomer, Aluminum Glycinate, Tartaric Acid, Titanium Dioxide, Hydrolyzed Collagen, Sodium Hyaluronate, Phosphatidylcholine, Adenosine, Ascorbic Acid, Silk Amino Acids

PURPOSE

Purpose: Skin Protectant

WARNINGS

Warnings: 1. If the following symptoms arise upon use of the cosmetic product, immediately discontinue use and consult a dermatologist, for continued use may aggravate the symptoms. A. Redness, swelling, itchiness, stimulation, or other symptoms B. Occurrence of the above symptoms upon exposure to direct sunlight. 2. Do not use on areas with wounds, eczema, or dermatitis. 3. Caution for storing. A. Put the lid back after using it. B. Keep it out of infants or children’s reach C. Don’t Keep it in the place where the temperature is extremely hot or cold and exposed to the direct sunlight D. Avoid using around the eye area.

KEEP OUT OF REACH OF CHILDREN

Keep it out of infants or children’s reach

INDICATIONS & USAGE

Indications & Usage: 1. After washing, prepare for mask treatment and tone skin by moisturizing your skin 2. Wear the mask sheet (upper), follow the cutting leave the eyes a space - How to put ear-hold patch- Place the sheet cutting line down. (It can be torn if you pull too much) 3. Take out the mask sheet from the package and remove protecting film. Hold the edges of sheet flat-side up. Pull the sheet gently to both sides along your face line and hook around your ears. 4. Leave the mask 10 to 20 minutes and take it off. 5. Massage and dab the face gently let the essence absorb into skin cell well.

DOSAGE & ADMINISTRATION

Dosage & Administration: Use immediately after opening. 2-3 times a week.